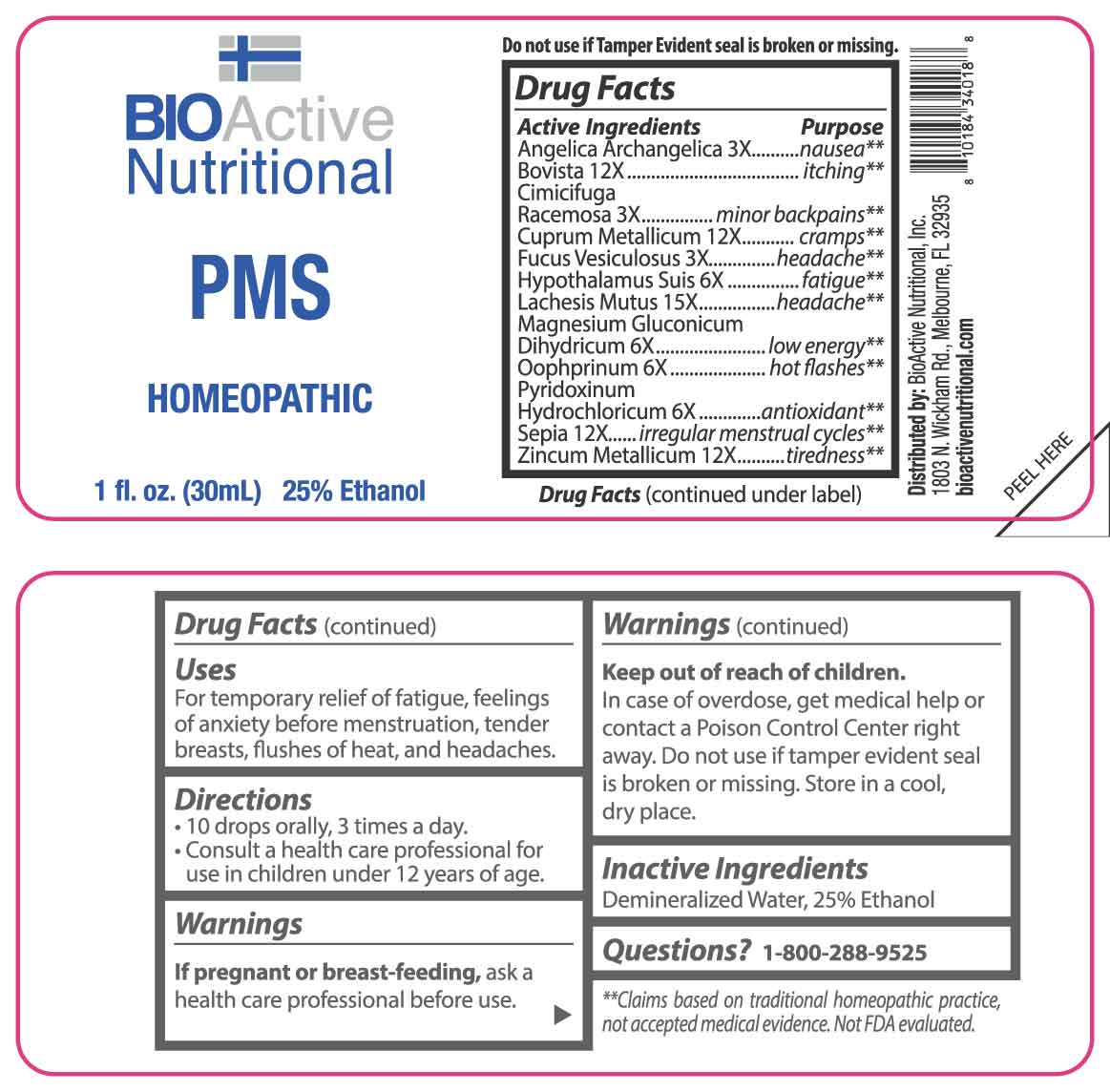 DRUG LABEL: PMS
NDC: 43857-0314 | Form: LIQUID
Manufacturer: BioActive Nutritional, Inc.
Category: homeopathic | Type: HUMAN OTC DRUG LABEL
Date: 20250402

ACTIVE INGREDIENTS: ANGELICA ARCHANGELICA ROOT 3 [hp_X]/1 mL; BLACK COHOSH 3 [hp_X]/1 mL; FUCUS VESICULOSUS 3 [hp_X]/1 mL; SUS SCROFA HYPOTHALAMUS 6 [hp_X]/1 mL; MAGNESIUM GLUCONATE 6 [hp_X]/1 mL; SUS SCROFA OVARY 6 [hp_X]/1 mL; PYRIDOXINE HYDROCHLORIDE 6 [hp_X]/1 mL; LYCOPERDON UTRIFORME FRUITING BODY 12 [hp_X]/1 mL; COPPER 12 [hp_X]/1 mL; SEPIA OFFICINALIS JUICE 12 [hp_X]/1 mL; ZINC 12 [hp_X]/1 mL; LACHESIS MUTA VENOM 15 [hp_X]/1 mL
INACTIVE INGREDIENTS: WATER; ALCOHOL

DRUG FACTS:

ACTIVE INGREDIENTS:

Angelica Archangelica 3X, Bovista 12X, Cimicifuga Racemosa 3X, Cuprum Metallicum 12X, Fucus Vesiculosus 3X, Hypothalamus Suis 6X, Lachesis Mutus 15X, Magnesium Gluconicum Dihydricum 6X, Oophorinum 6X, Pyridoxinum Hydrochloricum 6X, Sepia 12X, Zincum Metallicum 12X.

PURPOSE:

Angelica Archangelica - nausea,** Bovista - itching,** Cimicifuga Racemosa – minor backpains,** Cuprum Metallicum - cramps,** Fucus Vesiculosus - headache,** Hypothalamus Suis - fatigue,** Lachesis Mutus - headache,** Magnesium Gluconicum Dihydricum – low energy,** Oophorinum – hot flashes,** Pyridoxinum Hydrochloricum - antioxidant,** Sepia – irregular menstrual cycles,** Zincum Metallicum – tiredness**

**Claims based on traditional homeopathic practice, not accepted medical evidence. Not FDA Evaluated.

USES:

For temporary relief of fatigue, feelings or anxiety before menstruation, tender breasts, flushes of heat, and headaches.

WARNINGS:

If pregnant or breast-feeding, ask a health care professional before use.

Keep out of reach of children. In case of overdose, get medical help or contact a Poison Control Center right away.

Do not use if tamper evident seal is broken or missing.

Store in a cool, dry place.

KEEP OUT OF REACH OF CHILDREN:

In case of overdose, get medical help or contact a Poison Control Center right away.

DIRECTIONS:

• 10 drops orally, 3 times a day.

• Consult a health care professional for use in children under 12 years of age.

INACTIVE INGREDIENTS:

Demineralized Water, 25% Ethanol

QUESTIONS:

Distributed by:
BioActive Nutritional, Inc.
1803 N. Wickham Rd.
Melbourne, FL 32935
bioactivenutritional.com

1-800-288-9525

PACKAGE LABEL DISPLAY:

BIOActive Nutritional

PMS

HOMEOPATHIC

1 FL OZ (30 ml)